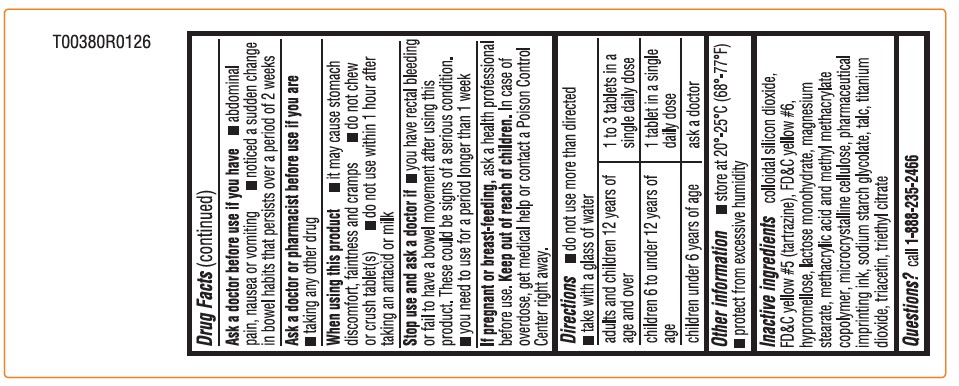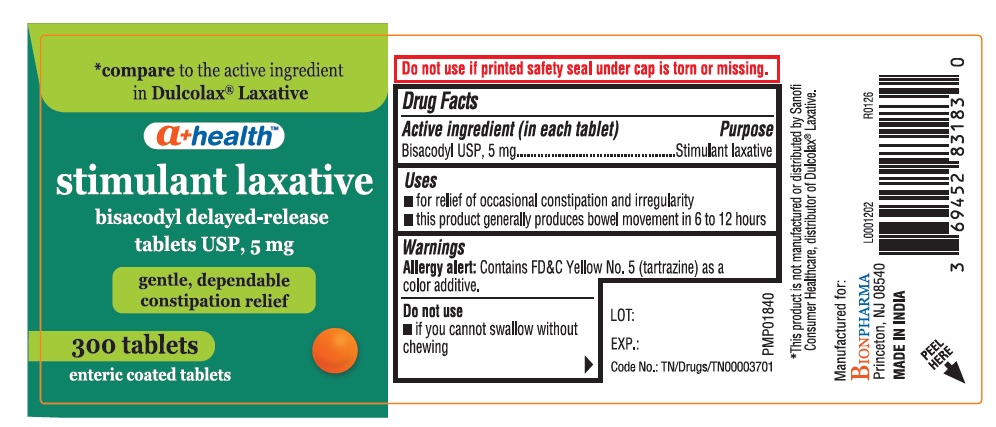 DRUG LABEL: stimulant laxative
NDC: 69452-541 | Form: TABLET, DELAYED RELEASE
Manufacturer: BIONPHARMA INC.
Category: otc | Type: HUMAN OTC DRUG LABEL
Date: 20260222

ACTIVE INGREDIENTS: BISACODYL 5 mg/1 1
INACTIVE INGREDIENTS: SODIUM STARCH GLYCOLATE TYPE A; SILICON DIOXIDE; FD&C YELLOW NO. 5; FD&C YELLOW NO. 6; METHACRYLIC ACID - METHYL METHACRYLATE COPOLYMER (1:1); HYPROMELLOSE, UNSPECIFIED; TALC; TITANIUM DIOXIDE; TRIACETIN; MICROCRYSTALLINE CELLULOSE; TRIETHYL CITRATE; MAGNESIUM STEARATE; LACTOSE MONOHYDRATE

a+ health-bisacodyl DR tablets 5 mg-stimulant laxative

Active ingredient (in each tablet)

Bisacodyl USP, 5 mg

Purpose

Stimulant laxative

Uses

■ for relief of occasional constipation and irregularity
■ this product generally produces bowel movement in 6 to 12 hours

Warnings

Allergy alert: Contains FD&C Yellow No. 5 (tartrazine) as a color additive.

Do not use

■ if you cannot swallow without chewing

Ask a doctor before use if you have

■ abdominal pain, nausea or vomiting ■ noticed a sudden change in bowel habits that persists over a period of 2 weeks

Ask a doctor or pharmacist before use if you are

■ taking any other drug

When using this product

■ it may cause stomach discomfort, faintness and cramps ■ do not chew or crush tablet(s) ■ do not use within 1 hour after
taking an antacid or milk

Stop use and ask a doctor if

■ you have rectal bleeding or fail to have a bowel movement after using this product. These could be signs of a serious condition.
■ you need to use for a period longer than 1 week

If pregnant or breast-feeding,

ask a health professional before use.

Keep out of reach of children.

In case of overdose, get medical help or contact a Poison Control Center right away.

Directions

■ do not use more than directed
■ take with a glass of water

adults and children 12 years of age and over | 1 to 3 tablets in a single daily dose
children 6 to under 12 years of age | 1 tablet in a single daily dose
children under 6 years of age | ask a doctor

Other information

■ store at 20°-25°C (68°-77°F)
■ protect from excessive humidity

Inactive ingredients

colloidal silicon dioxide, FD&C yellow #5 (tartrazine), FD&C yellow #6, hypromellose, lactose monohydrate, magnesium stearate, methacrylic acid and methyl methacrylate copolymer, microcrystalline cellulose, pharmaceutical imprinting ink, sodium starch glycolate, talc, titanium dioxide, triacetin, triethyl citrate

Questions?

call 1-888-235-2466

300's count

* compare to the active ingredient in Dulcolax® Laxative

a+ healthTM

stimulant laxative

bisacodyl delayed-release
tablets USP, 5 mg

gentle, dependable
constipation relief

300 tablets

enteric coated tablets